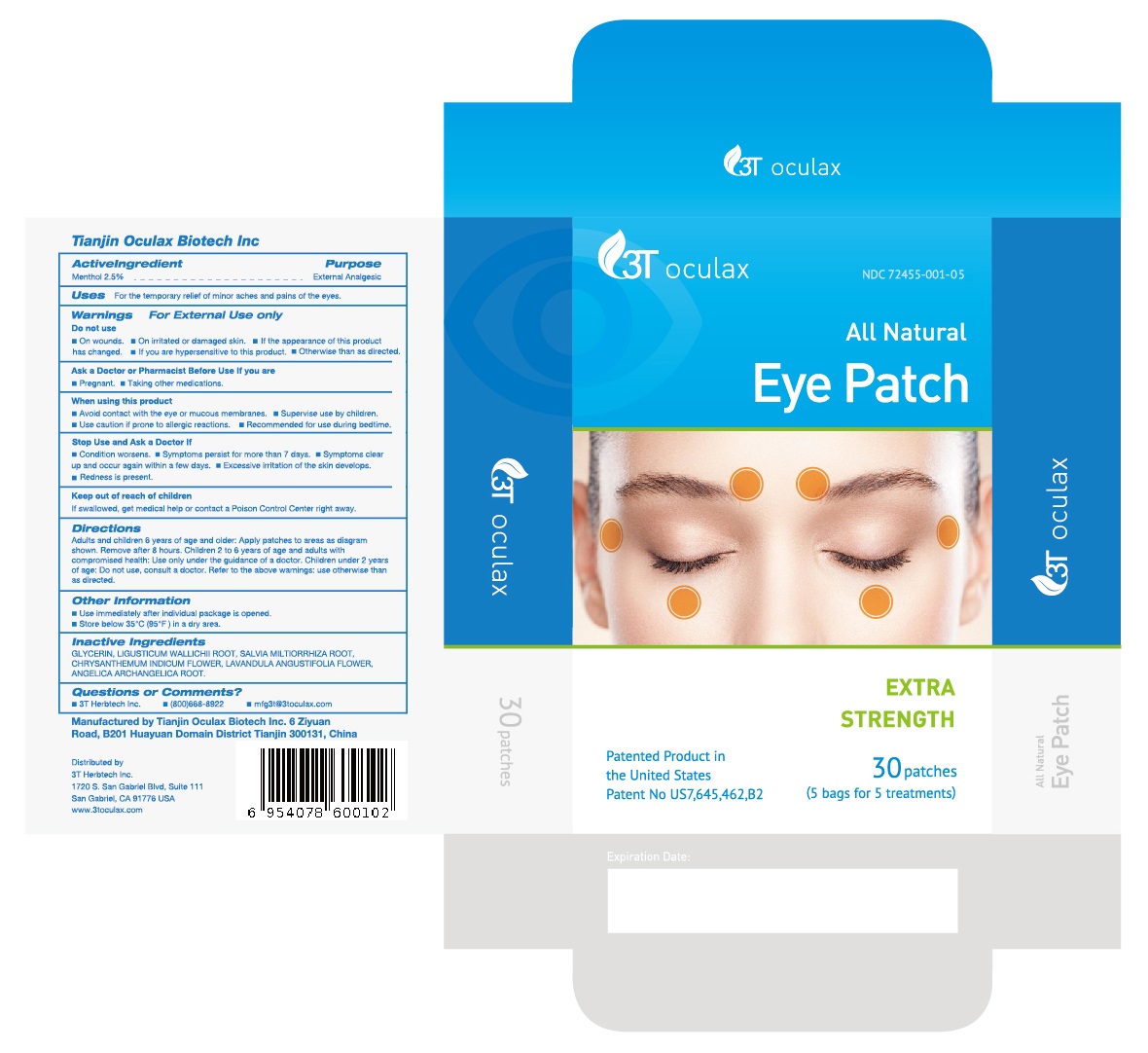 DRUG LABEL: All Natural Eye Patch
NDC: 72455-001 | Form: PATCH
Manufacturer: Tianjin Oculax Biotech Inc
Category: otc | Type: HUMAN OTC DRUG LABEL
Date: 20231226

ACTIVE INGREDIENTS: MENTHOL 2.5 mg/100 mg
INACTIVE INGREDIENTS: GLYCERIN; LIGUSTICUM WALLICHII ROOT; SALVIA MILTIORRHIZA ROOT; CHRYSANTHEMUM INDICUM FLOWER; LAVANDULA ANGUSTIFOLIA FLOWER; ANGELICA ARCHANGELICA ROOT

Tianjin Oculax Biotech Inc

ACTIVE INGREDIENT

Menthol 2.5%

PURPOSE

Menthol External Analgesic

USES

For the temporary relief of minor aches and pains of the eyes.

Warnings

For External Use only.

Do not use

on wounds.
on irritated or damaged skin.
if the appearance of this product has changed.
if you are hypersensitive to this product.
otherwise than as directed.

Ask a Doctor or Pharmacist Before Use If you are

pregnant.
taking other medications.

When using this product

avoid contact with the eye or mucous membranes.
supervise use by children.
use caution if prone to allergic reactions.

Stop Use and Ask a Doctor If

condition worsens.
symptoms persist for more than 7 days.
symptoms clear up and occur again within a few days.
excessive irritation of the skin develops.
redness is present.

Keep out of reach of children.

If swallowed, get medical help or contact a Poison Control Center right away.

Directions

Adults and children 6 years of age and older: Apply patches to areas as diagram shown. Remove after 8 hours. Children 2 to 6 years of age and adults with compromised health: Use only under the guidance of a doctor. Children under 2 years of age: Do not use, consult a doctor. Refer to the above warnings: use otherwise than as directed.

Other Information

Use immediately after individual package is opened.
Store below 35 ℃ (95 ℉) in a dry area.

Inactive Ingredients

GLYCERIN, LIGUSTICUM WALLICHII ROOT, SALVIA MILTIORRHIZA ROOT, CHRYSANTHEMUM INDICUM FLOWER, LAVANDULA ANGUSTIFOLIA FLOWER, ANGELICA ARCHANGELICA ROOT

Questions or Comments?

3T Herbtech Inc.
(800)668-8922
mfg3t@3t-herb.com

Manufactured byTianjin Oculax Biotech Inc 6 Ziyuan Road, B201 Huayuan Domain DistrictTianjin 300131, China

Distributed by

3T Herbtech Inc.
1720 S. San Gabriel Blvd, Suite 111
San Gabriel, CA 91776 USA